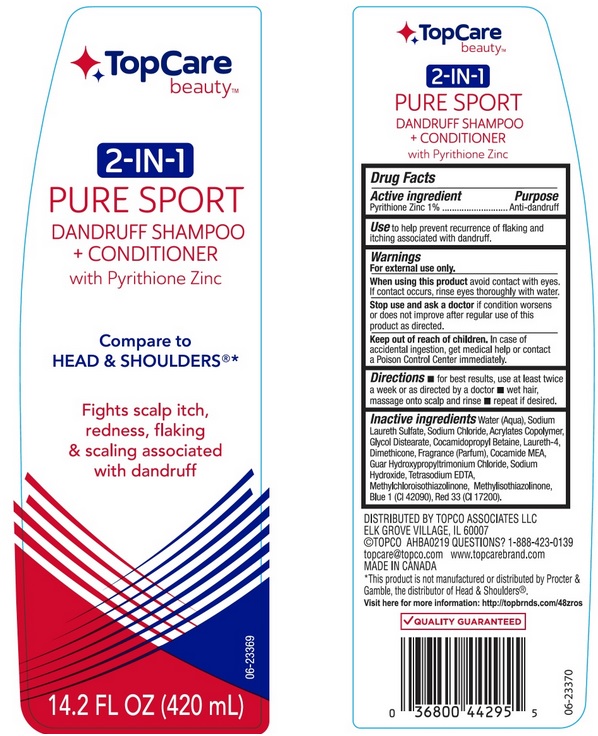 DRUG LABEL: TopCare Beauty Pure Sport Dandruff
NDC: 36800-433 | Form: SHAMPOO
Manufacturer: TopCo Associates LLC
Category: otc | Type: HUMAN OTC DRUG LABEL
Date: 20190508

ACTIVE INGREDIENTS: PYRITHIONE ZINC 10 mg/1 mL
INACTIVE INGREDIENTS: WATER; SODIUM LAURETH SULFATE; SODIUM CHLORIDE; METHACRYLIC ACID - METHYL METHACRYLATE COPOLYMER (1:1); GLYCOL DISTEARATE; COCAMIDOPROPYL BETAINE; LAURETH-4; DIMETHICONE; COCO MONOETHANOLAMIDE; GUAR HYDROXYPROPYLTRIMONIUM CHLORIDE (1.7 SUBSTITUENTS PER SACCHARIDE); SODIUM HYDROXIDE; EDETATE SODIUM; METHYLCHLOROISOTHIAZOLINONE; METHYLISOTHIAZOLINONE; FD&C BLUE NO. 1; D&C RED NO. 33

Drug Facts

Active ingredient

Pyrithione Zinc 1%

Purpose

Anti-dandruff

Use

to help prevent recurrence of flaking and itching associated with dandruff.

Warnings

For external use only.

When using this product

avoid contact with eyes. If contact occurs, rinse eyes thoroughly with water.

Stop use and ask a doctor if

condition worsens or does not improve after regular use of this product as directed.

Keep out of reach of children.

In case of accidental ingestion, get medical help or contact a Poison Control Center immediately.

Directions

- for best results, use at least twice a week or as directed by a doctor
- wet hair, massage onto scalp and rinse
- repeat if desired

Inactive ingredients

Water (Aqua), Sodium Laureth Sulfate, Sodium Chloride, Acrylates Copolymer, Glycol Distearate, Cocamidopropyl Betaine, Laureth-4, Dimethicone, Fragrance (Parfum), Cocamide MEA, Guar Hydroxypropyltrimonium Chloride, Sodium Hydroxide, Tetrasodium EDTA, Methylchloroisothiazolinone, Methylisothiazolinone, Blue 1 (CI 42090), Red 33 (CI 17200).